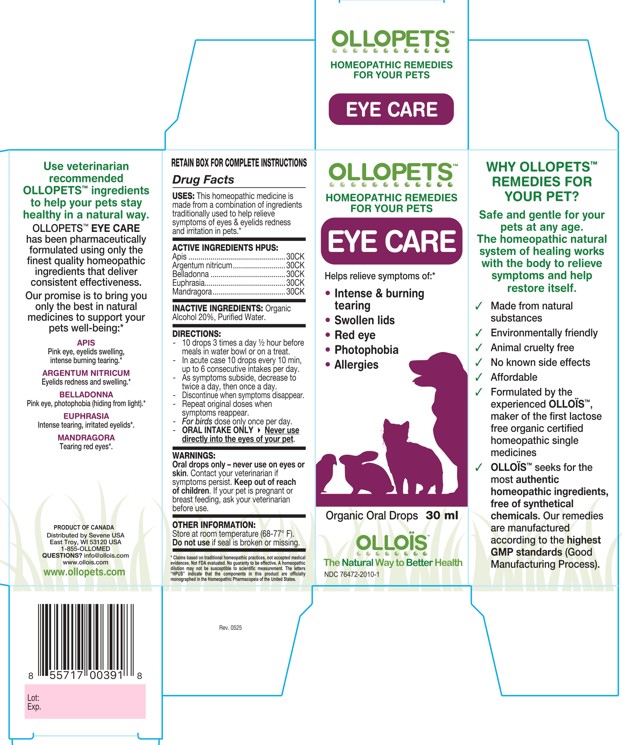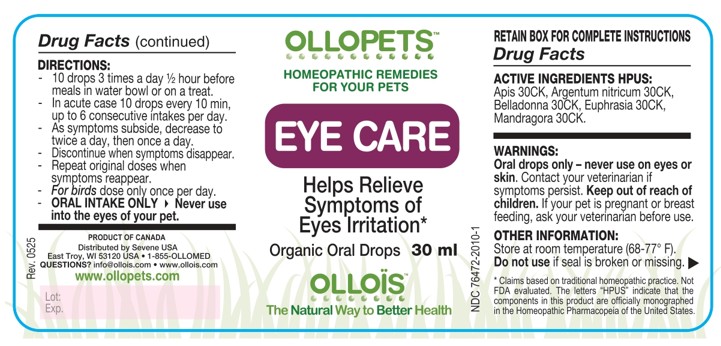 DRUG LABEL: OLLOPETS EYE CARE
NDC: 76472-2010 | Form: SOLUTION
Manufacturer: SEVENE USA
Category: homeopathic | Type: OTC ANIMAL DRUG LABEL
Date: 20260218

ACTIVE INGREDIENTS: APIS MELLIFERA 30 [hp_C]/100 mL; SILVER NITRATE 30 [hp_C]/100 mL; ATROPA BELLADONNA 30 [hp_C]/100 mL; EUPHRASIA STRICTA 30 [hp_C]/100 mL; MANDRAGORA OFFICINARUM ROOT 7 [hp_C]/100 mL
INACTIVE INGREDIENTS: ALCOHOL; WATER

SEVENE USA - OLLOPETS - EYE CARE

ACTIVE INGREDIENT HPUS

Apis ................................................30CK
Argentum nitricum..........................30CK
Belladonna .....................................30CK
Euphrasia........................................30CK
Mandragora....................................30CK